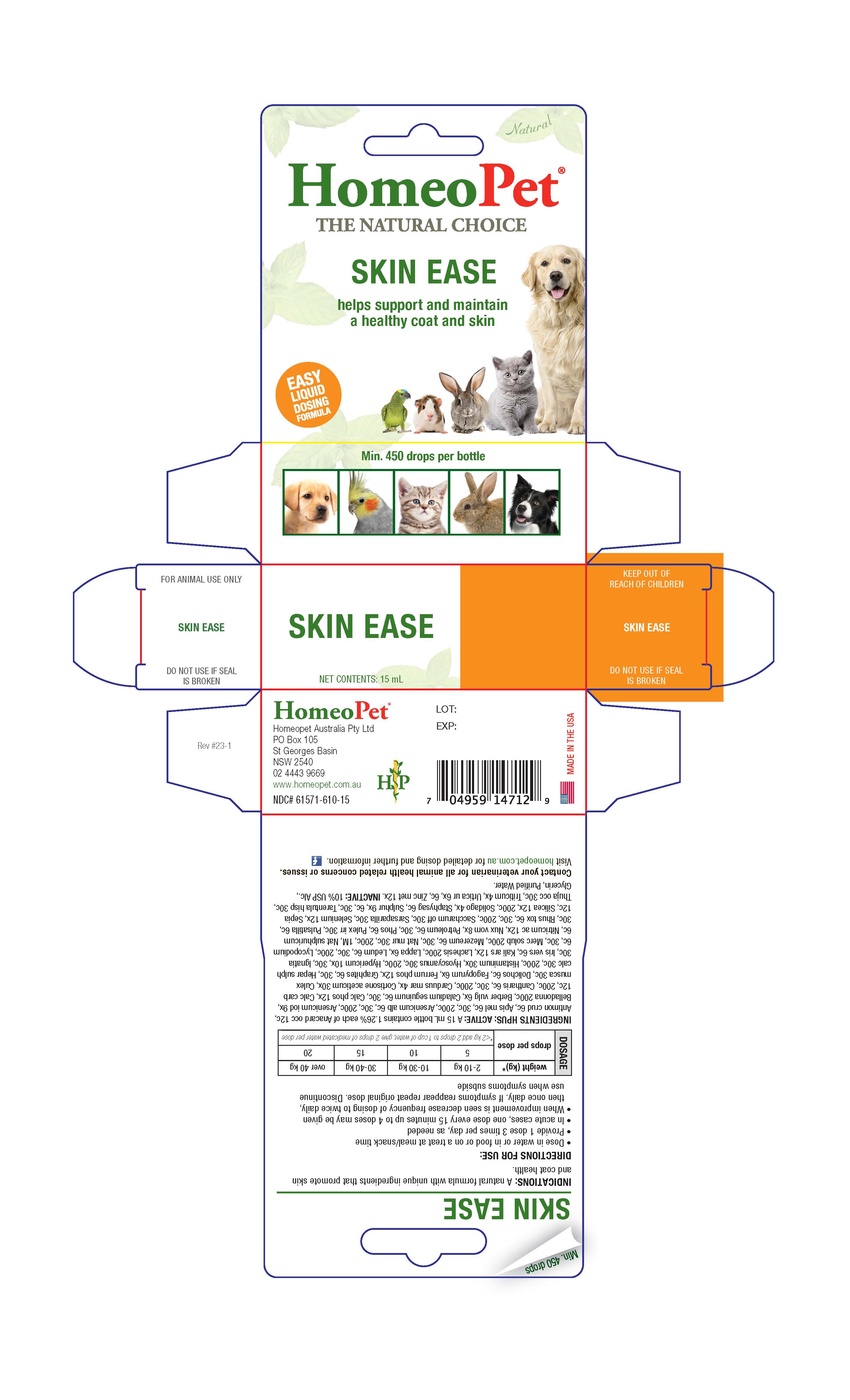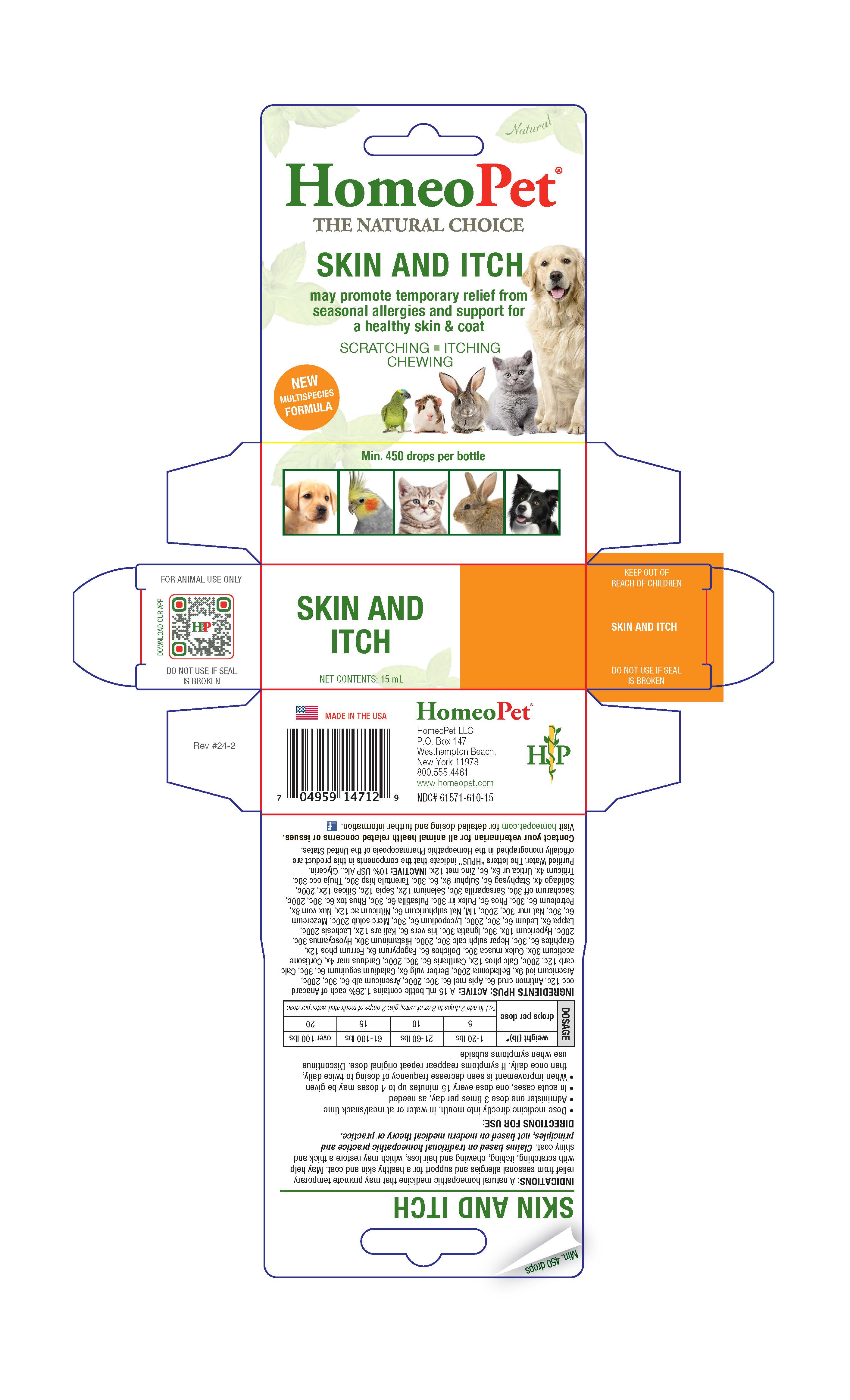 DRUG LABEL: Skin and Itch 
NDC: 61571-610 | Form: LIQUID
Manufacturer: HomeoPet, LLC
Category: homeopathic | Type: OTC ANIMAL DRUG LABEL
Date: 20251216

ACTIVE INGREDIENTS: ANACARDIUM OCCIDENTALE FRUIT 12 [hp_C]/15 mL; ANTIMONY TRISULFIDE 6 [hp_C]/15 mL; APIS MELLIFERA 6 [hp_C]/15 mL; ARSENIC TRIOXIDE 6 [hp_C]/15 mL; ARSENIC TRIIODIDE 9 [hp_X]/15 mL; ATROPA BELLADONNA 200 [hp_C]/15 mL; BERBERIS VULGARIS ROOT BARK 6 [hp_X]/15 mL; DIEFFENBACHIA SEGUINE WHOLE 6 [hp_C]/15 mL; TRIBASIC CALCIUM PHOSPHATE 12 [hp_X]/15 mL; OYSTER SHELL CALCIUM CARBONATE, CRUDE 12 [hp_C]/15 mL; LYTTA VESICATORIA 6 [hp_C]/15 mL; MILK THISTLE 4 [hp_X]/15 mL; CORTISONE ACETATE 30 [hp_X]/15 mL; CULEX PIPIENS 30 [hp_C]/15 mL; MUCUNA PRURIENS FRUIT TRICHOME 6 [hp_C]/15 mL; FAGOPYRUM ESCULENTUM WHOLE 6 [hp_X]/15 mL; FERROSOFERRIC PHOSPHATE 12 [hp_X]/15 mL; GRAPHITE 6 [hp_C]/15 mL; CALCIUM SULFIDE 30 [hp_C]/15 mL; HISTAMINE DIHYDROCHLORIDE 30 [hp_X]/15 mL; HYOSCYAMUS NIGER 30 [hp_C]/15 mL; HYPERICUM PERFORATUM WHOLE 10 [hp_X]/15 mL; STRYCHNOS IGNATII SEED 30 [hp_C]/15 mL; IRIS VERSICOLOR ROOT 6 [hp_C]/15 mL; POTASSIUM ARSENITE ANHYDROUS 12 [hp_X]/15 mL; LACHESIS MUTA VENOM 200 [hp_C]/15 mL; ARCTIUM LAPPA ROOT 6 [hp_X]/15 mL; RHODODENDRON TOMENTOSUM LEAFY TWIG 6 [hp_C]/15 mL; LYCOPODIUM CLAVATUM SPORE 6 [hp_C]/15 mL; MERCURIUS SOLUBILIS 200 [hp_C]/15 mL; DAPHNE MEZEREUM BARK 6 [hp_C]/15 mL; SODIUM CHLORIDE 30 [hp_C]/15 mL; SODIUM SULFATE 6 [hp_C]/15 mL; NITRIC ACID 12 [hp_X]/15 mL; STRYCHNOS NUX-VOMICA SEED 8 [hp_X]/15 mL; KEROSENE 6 [hp_C]/15 mL; PHOSPHORUS 6 [hp_C]/15 mL; PULEX IRRITANS WHOLE 30 [hp_C]/15 mL; PULSATILLA VULGARIS WHOLE 6 [hp_C]/15 mL; TOXICODENDRON PUBESCENS LEAF 6 [hp_C]/15 mL; SUCROSE 30 [hp_C]/15 mL; SMILAX ORNATA ROOT 30 [hp_C]/15 mL; SELENIUM 12 [hp_X]/15 mL; SEPIA OFFICINALIS JUICE 12 [hp_C]/15 mL; SILICON DIOXIDE 12 [hp_X]/15 mL; SOLIDAGO VIRGAUREA FLOWERING TOP 4 [hp_X]/15 mL; DELPHINIUM STAPHISAGRIA SEED 6 [hp_C]/15 mL; SULFUR 9 [hp_X]/15 mL; LYCOSA TARANTULA 30 [hp_C]/15 mL; THUJA OCCIDENTALIS LEAFY TWIG 30 [hp_C]/15 mL; ELYMUS REPENS ROOT 4 [hp_X]/15 mL; URTICA URENS WHOLE 6 [hp_X]/15 mL; ZINC 12 [hp_X]/15 mL
INACTIVE INGREDIENTS: ALCOHOL; GLYCERIN; WATER

Skin and Itch

Directions for Use and Dosage

DIRECTIONS FOR USE:

- Dose remedy directly into mouth, in water or at meal/snack time
- Administer one dose 3 times per day, as needed
- In acute cases, one dose every 15 minutes up to 4 doses may be given
- When improvement is seen decrease frequency of dosing to twice daily, then once daily. If symptoms reappear repeat original dose. Discontinue use when symptoms subside

Dosage | weight (lb)* | 1-20 lbs | 21-60 lbs | 61-100 lbs | over 100 lbs
Dosage | drops per dose | 5 | 10 | 15 | 20
Dosage | drops per dose | *<1 lb add 2 drops to 8 oz of water, give 2 drops of medicated water per dose

Contact Veterinarian

Contact your veterinarian for all animal health related concerns or issues.

Visit homeopet.com for detailed dosing and further information.

Ingredients HPUS: Active

Anacard occ 12c, Antimon crud 6c, Apis mel 6c, 30c, 200c, Arsenicum alb 6c, 30c, 200c, Arsenicum iod 9x, Belladonna 200c, Berber vulg 6x, Caladium seguinum 6c, 30c, Calc phos 12x, Calc carb 12c, 200c, Cantharis 6c, 30c, 200c, Carduus mar 4x, Cortisone aceticum 30x, Culex musca 30c, Dolichos 6c, Fagopyrum 6x, Ferrum phos 12x, Graphites 6c, 30c, Hepar sulph calc 30c, 200c, Histaminum 30x, Hyoscyamus 30c, 200c, Hypericum 10x, 30c, Ignatia 30c, Iris vers 6c, Kali ars 12x, Lachesis 200c, Lappa 6x, Ledum 6c, 30c, 200c, Lycopodium 6c, 30c, Merc solub 200c, Mezereum 6c, 30c, Nat mur 30c, 200c, 1M, Nat sulphuricum 6c, Nitricum ac 12x, Nux vom 8x, Petroleum 6c, 30c, Phos 6c, Pulex irr 30c, Pulsatilla 6c, 30c, Rhus tox 6c, 30c, 200c, Saccharum off 30c, Sarsaparilla 30c, Selenium 12x, Sepia 12c, Silicea 12x, 200c, Solidago 4x, Staphysag 6c, Sulphur 9x, 6c, 30c, Tarentula hisp 30c, Thuja occ 30c, Triticum 4x, Urtica ur 6x, 6c, Zinc met 12x.

Inactive Ingredients

USP Alcohol, Glycerin, Purified Water

Skin & Itch

may promote temporary relief from seasonal allergies and support for a a healthy skin & coat

SCRATCHING-ITCHING-CHEWING

Indications

A natural homeopathic medicine that may promote temporary relief from seasonal allergies and support for a healthy skin and coat. May help with scratching, itching, chewing and hair loss, which may restore a thick and shiny coat. Claims based on traditional homeopathic practice and principles, not based on modern medical theyory or practice.